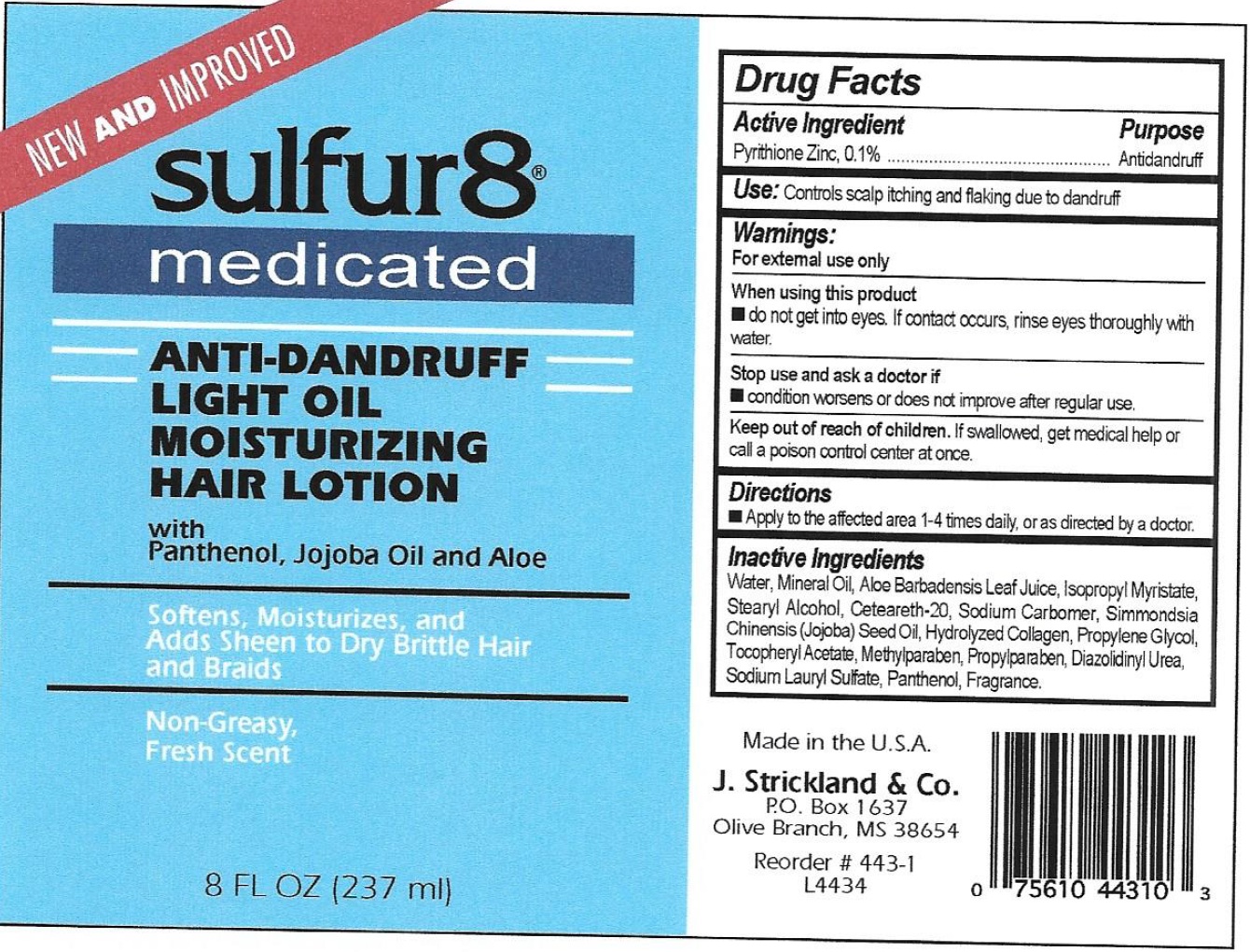 DRUG LABEL: Sulfur 8 Light Moisturizer Anti-Dandruff
NDC: 12022-020 | Form: LOTION
Manufacturer: J. Strickland & Co.
Category: otc | Type: HUMAN OTC DRUG LABEL
Date: 20231021

ACTIVE INGREDIENTS: PYRITHIONE ZINC 1 mg/1 mL
INACTIVE INGREDIENTS: WATER; MINERAL OIL; ALOE VERA LEAF; ISOPROPYL MYRISTATE; STEARYL ALCOHOL; POLYOXYL 20 CETOSTEARYL ETHER; JOJOBA OIL; PROPYLENE GLYCOL; .ALPHA.-TOCOPHEROL ACETATE; METHYLPARABEN; PROPYLPARABEN; DIAZOLIDINYL UREA; SODIUM LAURYL SULFATE; PANTHENOL

Sulfur 8 Light Oil Moisturizer Anti-Dandruff Lotion

Active Ingredients

Pyrithione Zinc, 0.1%

Purpose

Antidandruff

Use:

Controls scalp itching and flaking due to dandruff

Warnings:

For external use only

When using this product

- do not get into eyes. If contact occurs, rinse eyes thoroughly with water.

Stop use and consult a doctor if

- condition worsens or does not improve after regular use

Keep out of reach of children

If swallowed, get medical help or call a poison control center at once.

Directions

- Spray to apply to the affected area 1-4 times daily, or as directed by a doctor.

Inactive Ingredients

Water, Glycerin, PEG-12 Dimethicone, Propylene Glycol, Sodium Hydroxide, Hydrolyzed Collagen, Disodium EDTA, Diazolidinyl Urea, Fragrance, Methylparaben, Propylparaben.